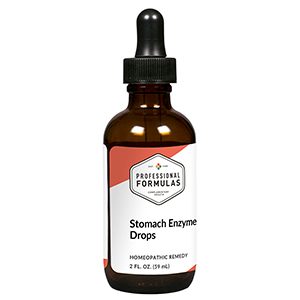 DRUG LABEL: Stomach Enzyme Drops
NDC: 63083-2093 | Form: LIQUID
Manufacturer: Professional Complementary Health Formulas
Category: homeopathic | Type: HUMAN OTC DRUG LABEL
Date: 20190815

ACTIVE INGREDIENTS: PANCRELIPASE AMYLASE 2 [hp_X]/59 mL; CELLULASE (TRICHODERMA LONGIBRACHIATUM) 2 [hp_X]/59 mL; PANCRELIPASE LIPASE 2 [hp_X]/59 mL; SODIUM PHOSPHATE, DIBASIC, HEPTAHYDRATE 2 [hp_X]/59 mL; PEPSIN 2 [hp_X]/59 mL; BETAINE HYDROCHLORIDE 6 [hp_X]/59 mL; TRIPE 6 [hp_X]/59 mL; COMFREY ROOT 6 [hp_X]/59 mL
INACTIVE INGREDIENTS: ALCOHOL; WATER

C93

ACTIVE INGREDIENTS

Amylase 2X
Cellulase 2X
Lipase 2X
Natrum phosphoricum 2X
Pepsinum 2X
Betainum muriaticum 6X
Stomach 6X
Symphytum officinale 6X

QUESTIONS

Professional Formulas

PO Box 2034 Lake Oswego, OR 97035

INDICATIONS

For the temporary relief of indigestion, gas, bloating, or mild abdominal pain or cramping.*

PURPOSE

*Claims based on traditional homeopathic practice, not accepted medical evidence. Not FDA evaluated.

WARNINGS

In case of overdose, get medical help or contact a poison control center right away.

Keep out of the reach of children.

PREGNANCY OR BREAST FEEDING

If pregnant or breastfeeding, ask a healthcare professional before use.

DIRECTIONS

Place drops under tongue 30 minutes before/after meals. Adults and children 12 years and over: Take 10 drops up to 3 times per day. Consult a physician for use in children under 12 years of age.

OTHER INFORMATION

Tamper resistant. If seal is broken, do not use. After opening, close container tightly and store at room temperature away from heat.

INACTIVE INGREDIENTS

20% ethanol, purified water.

LABEL

Est 1985

Professional Formulas

Complementary Health

Stomach Enzyme Drops

Homeopathic Remedy

2 FL. OZ. (59 mL)